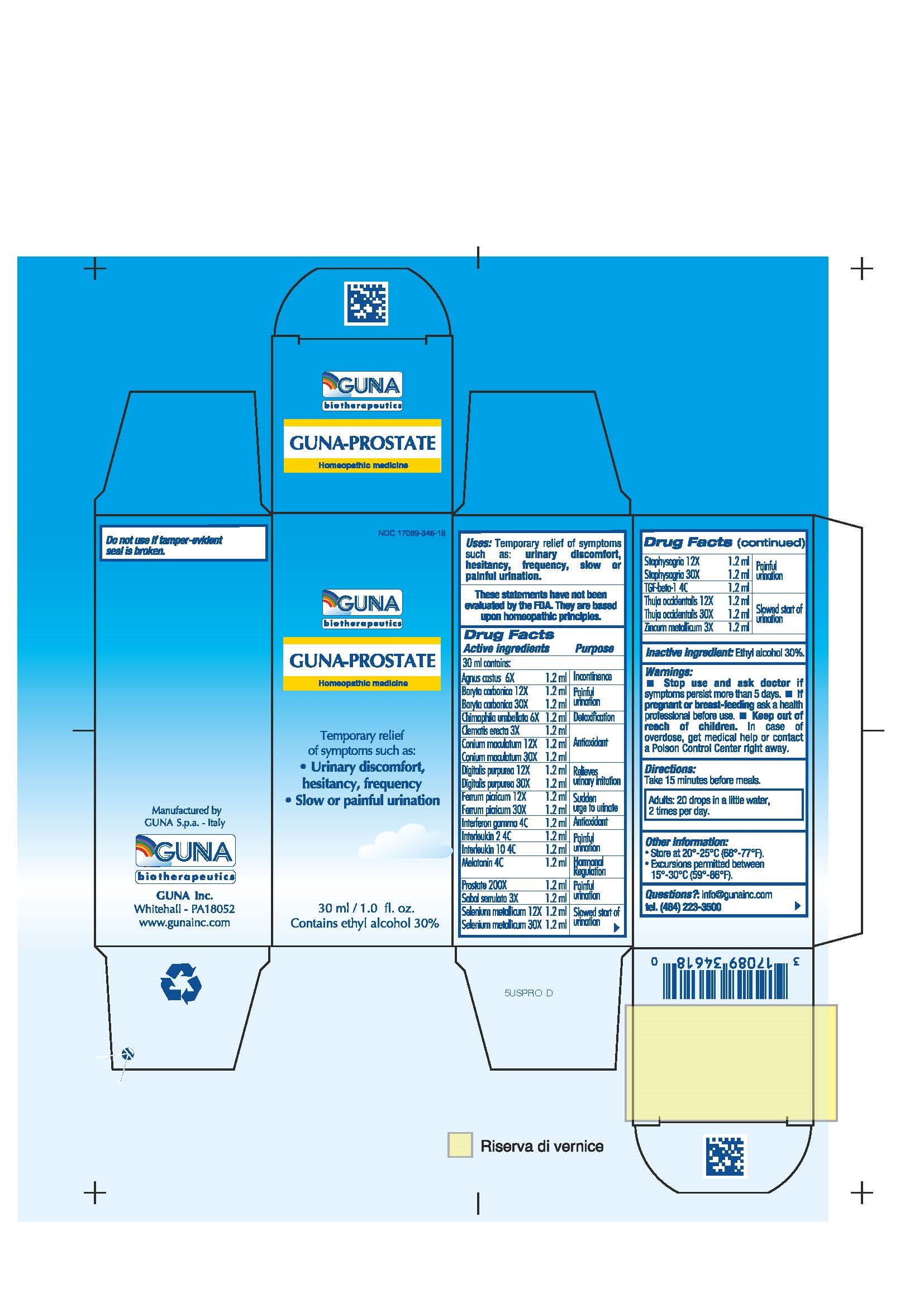 DRUG LABEL: GUNA-PROSTATE
NDC: 17089-346 | Form: SOLUTION/ DROPS
Manufacturer: Guna spa
Category: homeopathic | Type: HUMAN OTC DRUG LABEL
Date: 20181221

ACTIVE INGREDIENTS: FERRIC PICRATE 30 [hp_X]/30 mL; CHASTE TREE 6 [hp_X]/30 mL; BARIUM CARBONATE 30 [hp_X]/30 mL; CHIMAPHILA UMBELLATA 6 [hp_X]/30 mL; CLEMATIS RECTA FLOWERING TOP 3 [hp_X]/30 mL; CONIUM MACULATUM FLOWERING TOP 30 [hp_X]/30 mL; DIGITALIS 30 [hp_X]/30 mL; INTERFERON GAMMA-1B 4 [hp_C]/30 mL; INTERLEUKIN-10 4 [hp_C]/30 mL; ALDESLEUKIN 4 [hp_C]/30 mL; MELATONIN 4 [hp_C]/30 mL; SUS SCROFA PROSTATE 200 [hp_X]/30 mL; SAW PALMETTO 3 [hp_X]/30 mL; SELENIUM 30 [hp_X]/30 mL; DELPHINIUM STAPHISAGRIA SEED 30 [hp_X]/30 mL; TRANSFORMING GROWTH FACTOR BETA-1 4 [hp_C]/30 mL; THUJA OCCIDENTALIS LEAFY TWIG 30 [hp_X]/30 mL; ZINC 3 [hp_X]/30 mL
INACTIVE INGREDIENTS: ALCOHOL

GUNA-PROSTATE

ACTIVE INGREDIENTS/PURPOSE

AGNUS CASTUS 6X INCONTINENCE
BARYTA CARBONICA 12X 30X PAINFUL URINATION
CHIMAPHILA UMBELLATA 6X DETOXIFICATION
CLEMATIS ERECTA 3X ANTIOXIDANT
CONIUM MACULATUM 12X 30X ANTIOXIDANT
DIGITALIS PURPUREA 12X 30X RELIEVES URINARY IRRITATION
FERRUM PICRINICUM 12X 30X SUDDEN URGE TO URINATE
INTERFERON GAMMA 4C ANTIOXIDANT
INTERLEUKIN 10 4C PAINFUL URINATION
INTERLEUKIN 2 4C PAINFUL URINATION
MELATONIN 4C HORMONAL REGULATION
PROSTATE 200X PAINFUL URINATION
SABAL SERRULATA 3X PAINFUL URINATION
SELENIUM METALLICUM 12X 30X SLOWED START OF URINATION
STAPHYSAGRIA 12X 30X PAINFUL URINATION
TGF BETA 4C PAINFUL URINATION
THUJA OCCIDENTALIS 12X 30X SLOWED START OF URINATION
ZINCUM METALLICUM 3X SLOWED START OF URINATION

USES

Temporary relief of symptoms such as:

- Urinary disconfort, hesitancy, frequency
- Slow or painful urination

WARNINGS

- Stop use and ask doctor if symptoms persist more than 5 days or worsen.
- If pregnant or breast-feeding ask a health professional before use.
- Keep out of reach of children. In case of overdose, get medical help or contact a Poison Control Center right away.
- Contains ethyl alcohol 30%

PREGNANCY

If pregnant or breast-feeding ask a doctor before use

WARNINGS

Keep out of reach of children

DIRECTIONS

Take 15 minutes before meals
Adults: 20 drops in a little water, 2 times per day

QUESTIONS

Questions?: info@gunainc.com, tel. (484) 223-3500

Inactive ingredient: Ethyl alcohol 30%.

INDICATIONS AND USAGE

- Take 15 minutes before meals.

- indications and usage section